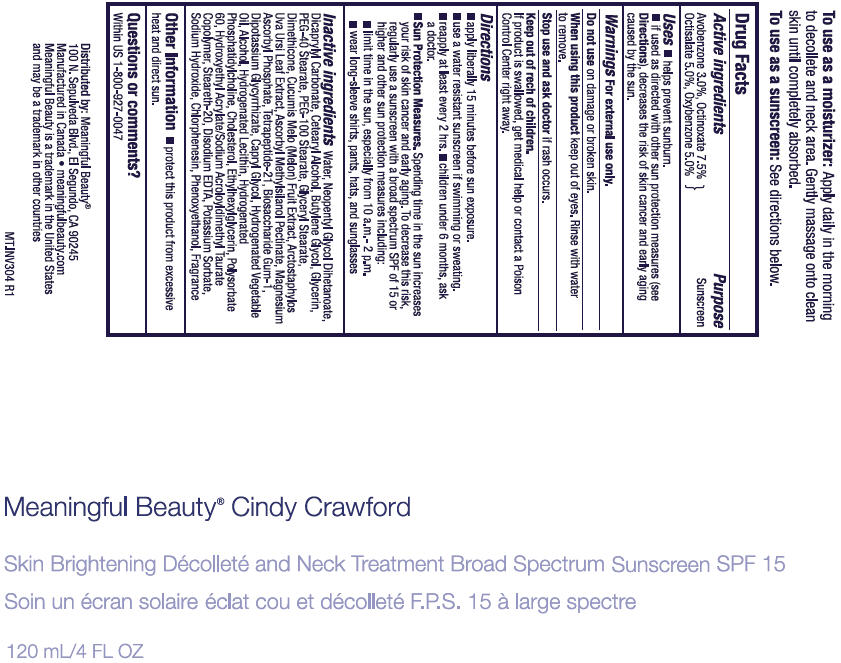 DRUG LABEL: Meaningful Beauty Cindy Crawford 
NDC: 70605-006 | Form: CREAM
Manufacturer: Guthy-Renker LLC
Category: otc | Type: HUMAN OTC DRUG LABEL
Date: 20220401

ACTIVE INGREDIENTS: AVOBENZONE 3 mg/100 mL; OCTINOXATE 7.5 mg/100 mL; OCTISALATE 5 mg/100 mL; OXYBENZONE 5 mg/100 mL
INACTIVE INGREDIENTS: WATER; NEOPENTYL GLYCOL DIHEPTANOATE; DICAPRYLYL CARBONATE; CETOSTEARYL ALCOHOL; BUTYLENE GLYCOL; GLYCERIN; PEG-40 STEARATE; PEG-100 STEARATE; GLYCERYL MONOSTEARATE; DIMETHICONE; MUSKMELON; ARCTOSTAPHYLOS UVA-URSI LEAF; MAGNESIUM ASCORBYL PHOSPHATE; TETRAPEPTIDE-21; BIOSACCHARIDE GUM-1; GLYCYRRHIZINATE DIPOTASSIUM; CAPRYLYL GLYCOL; ALCOHOL; CHOLESTEROL; ETHYLHEXYLGLYCERIN; POLYSORBATE 60; STEARETH-20; EDETATE DISODIUM; POTASSIUM SORBATE; SODIUM HYDROXIDE; CHLORPHENESIN; PHENOXYETHANOL

Meaningful Beauty® Cindy Crawford Skin Brightening Décolleté and Neck Treatment SPF 15

Drug Fact Label

Active ingredient

Avobenzone 3.0%, Octinoxate 7.5%, Octisalate 5.0%, Oxybenzone 5.0%

Purpose

Sunscreen

Uses

- helps prevent sunburn
- if used as directed with other sun protection measures (see Directions), decreases the risk of skin cancer and early aging caused by the sun.

Warnings

For external use only.

Do not use on damage or broken skin.

When using this product this product keep out of eyes. Rinse with water to remove.

Stop use and ask a doctor if rash occurs.

Keep out of reach of children. If product is swallowed, get medical help or contact a Poison Control Center right away.

Directions

- apply liberally 15 minutes before sun exposure.
- Use a water resistant sunscreen if swimming or sweating.
- Reapply at least every 2 hrs.
- children under 6 months, ask a doctor.
- Sun Protection Measures. Spending time in the sun increases your risk of skin cancer early aging. To decrease this risk, regularly use a sunscreen with a broad spectrum SPF of 15 or higher and other sun protection measures including:
  - Limit time in the sun, especially from 10 a.m.-2 p.m.
  - Wear long-sleeve shirts, pants, hats, and sunglasses

Inactive ingredients

Water, Neopentyl Glycol Diheptanoate, Dicaprylyl Carbonate, Cetearyl Alcohol, Butylene Glycol, Glycerin, PEG-40 Stearate, PEG-100 Stearate, Glyceryl Stearate, Dimethicone, Cucumis Melo (Melon) Fruit Extract, Arctostaphylos Uva Ursi Leaf Extract, Ascorbyl Methylsilanol Pectinate, Magnesium Ascorbyl Phosphate, Tetrapeptide-21, Biosaccharide Gum-1, Dipotassium Glycyrrhizate, Caprylyl Glycol, Hydrogenated Vegetable Oil, Alcohol, Hydrogenated Lecithin, Hydrogenated Phosphatidylcholine, Cholesterol, Ethylhexylglycerin, Polysorbate 60, Hydroxyethyl Acrylate/Sodium Acryloyldimethyl Taurate Copolymer, Steareth-20, Disodium EDTA, Potassium Sorbate, Sodium Hydroxide, Chlorphenesin, Phenoxyethanol, Fragrance.

Questions or comments?

Within US 1-800-927-0047

Distributed by: Meaningful Beauty®
100 N. Sepulveda Blvd., El Segundo, CA 90245

PRINCIPAL DISPLAY PANEL - 120 mL Tube Label

Meaningful Beauty® Cindy Crawford

Skin Brightening Décolleté and Neck Treatment Broad Spectrum Sunscreen SPF 15

120 mL/4 FL OZ